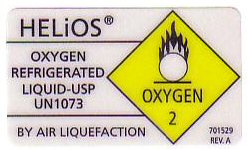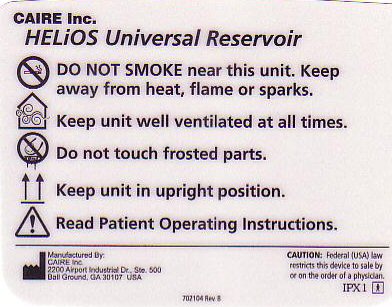 DRUG LABEL: OXYGEN
NDC: 59704-0001 | Form: GAS
Manufacturer: ALA Med dba Pulmonary Care Services
Category: prescription | Type: HUMAN PRESCRIPTION DRUG LABEL
Date: 20200101

ACTIVE INGREDIENTS: OXYGEN 99 L/100 L

PRODUCT WARNINGS AND PRECAUTIONS

DO NOT SMOKE NEAR THIS UNIT. KEEP AWAY FROM HEAT, FLAME OR SPARKS. KEEP UNIT WELL VENTILATED AT ALL TIMES. DO NOT TOUCH FROSTED PARTS. KEEP UNIT IN UPRIGHT POSITION. READ PATIENT OPERATING INSTRUCTIONS.

UNIT LABELS

HELIOS OXYGEN REFRIGERATED LIQUID USP OXYGEN - 2

BY AIR LIQUEFACTION 7051529 REV A

CAIRE HELIOS UNIVERSAL RESERVOIR

CAUTION: FEDERAL (USA) LAW RESTRICTS THIS DEVICE TO SALE BY OR ON THE ORDER OF A PHYSICAN

IPX 1 MANUFACTURED BY CAIRE INC. 2200 AIRPORT INDUSTRIAL DRIVE STE 500 BALL GROUND, GA 30107 USE - 702104 REV B

res